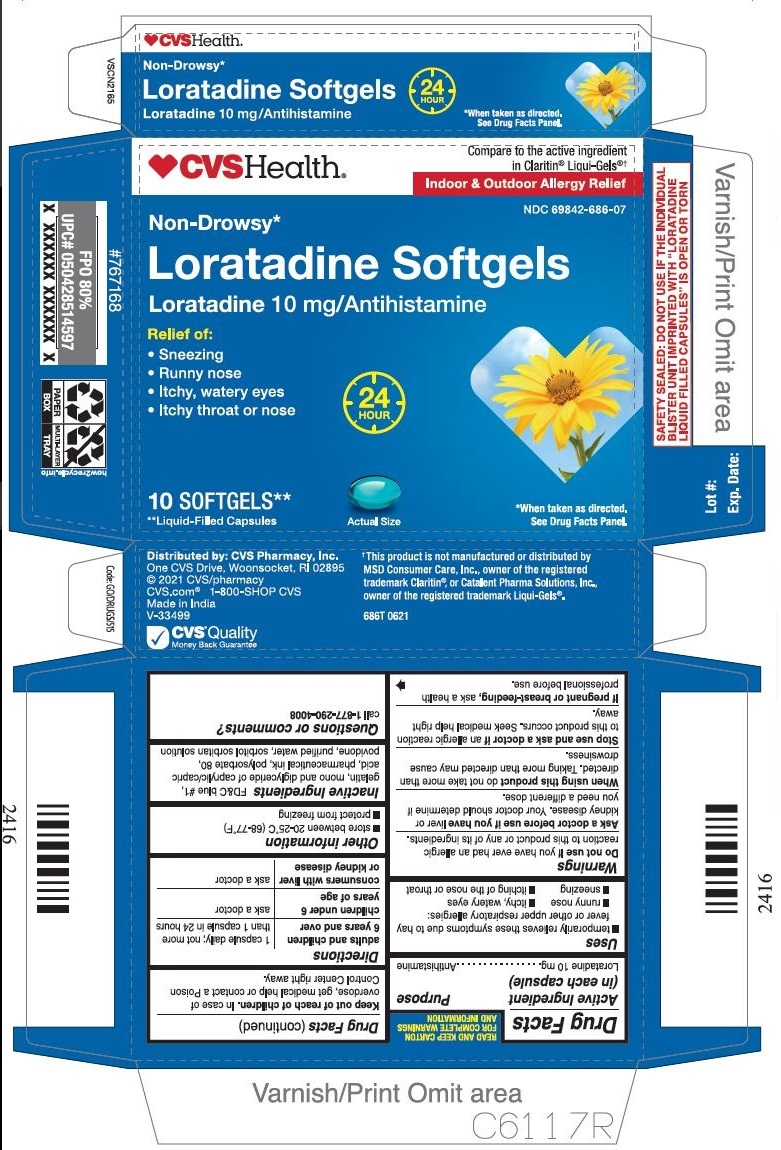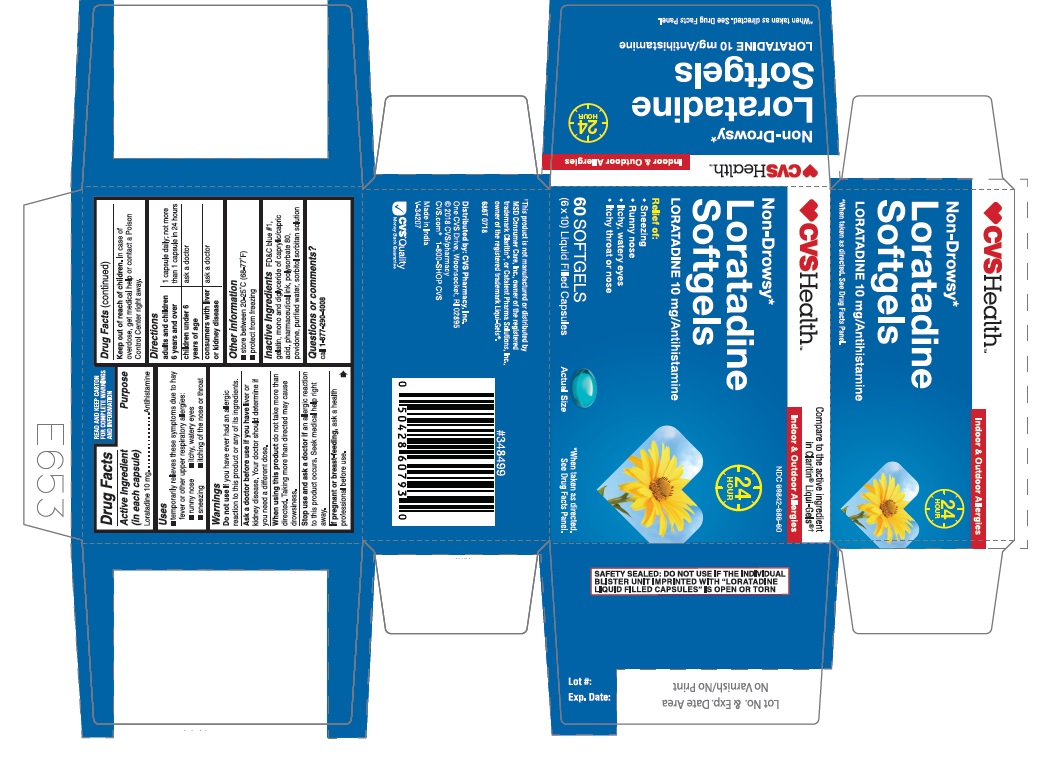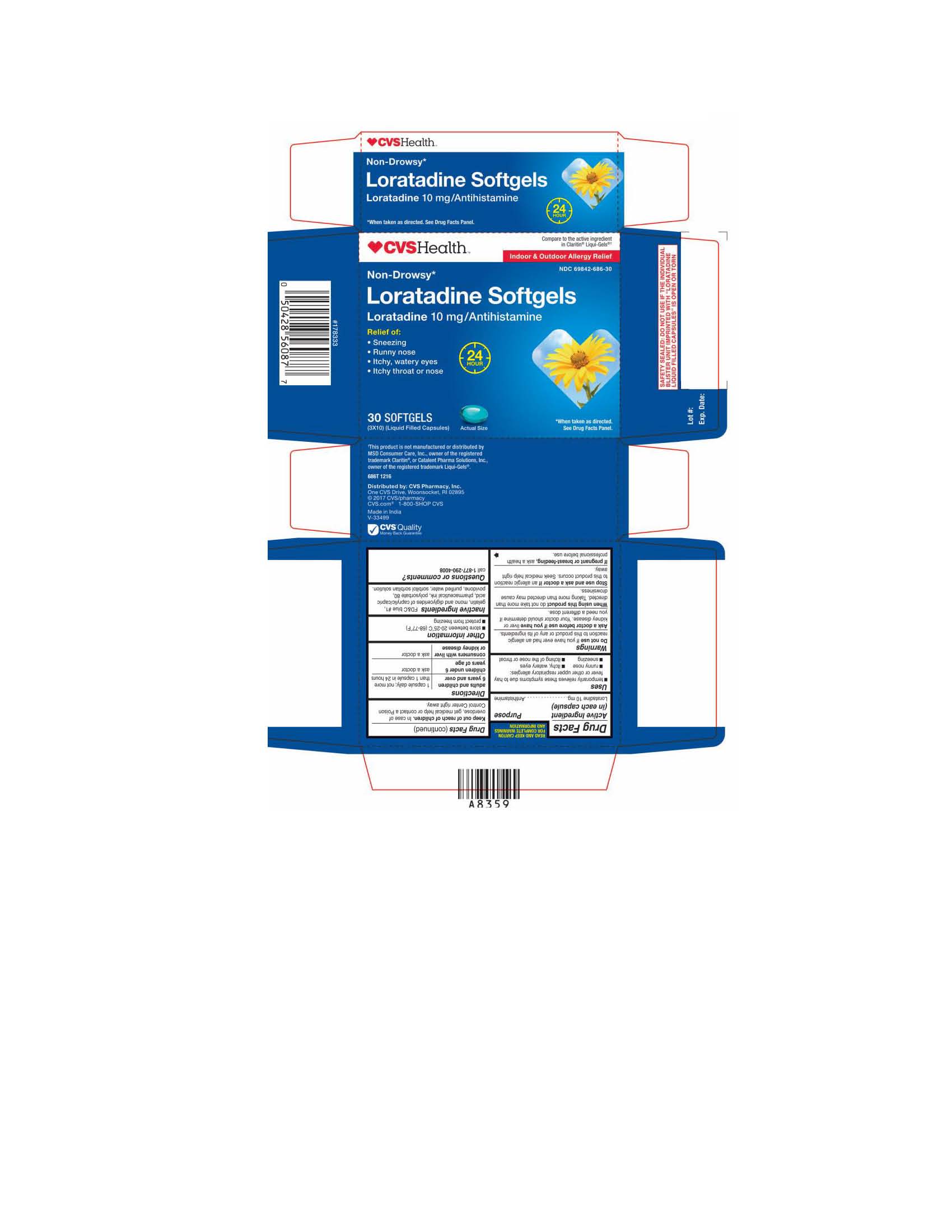 DRUG LABEL: LORATADINE
NDC: 69842-686 | Form: CAPSULE, LIQUID FILLED
Manufacturer: CVS HEALTH CORP
Category: otc | Type: HUMAN OTC DRUG LABEL
Date: 20221111

ACTIVE INGREDIENTS: LORATADINE 10 mg/1 1
INACTIVE INGREDIENTS: FD&C BLUE NO. 1; GELATIN; POLYSORBATE 80; POVIDONE; WATER; SORBITOL; CAPRYLIC/CAPRIC MONO/DIGLYCERIDES

686T CVS 69842 686 Loratadine Softgels 10 mg

Active Ingredient (in each capsule)

Loratadine 10 mg

Purpose

Antihistamine

Uses

temporarily relieves these symptoms due to hay fever or other upper respiratory allergies:

- runny nose
- itchy, watery eyes
- sneezing
- itching of the nose or throat

Warnings

Do not use If you have ever had an allergic reaction to this product or any of its ingredients.

Ask a doctor before use if you have liver or kidney disease. Your doctor should determine if you need a different dose.

When using this product do not take more than directed. Taking more than directed may cause drowsiness.

Stop use and ask a doctor if an allergic reaction to this product occurs, Seek medical help right away.

PREGNANCY OR BREAST FEEDING

If pregnant or breast-feeding, ask a health professional before use.

Keep out of reach of children. In case of overdose, get medical help or contact a Poison Control Center right away.

Directions

- adults and children 6 years and over: 1 capsule daily; not more than 1 capsule in 24 hours
- children under 6 years of age: ask a doctor
- consumers with liver or kidney disease: ask a doctor

Other information

• store between 20-25°C (68-77°F)
• protect from freezing

INACTIVE INGREDIENT

Inactive Ingredients FD&C blue # 1, gelatin, mono and diglyceride of caprylic/capric acid, pharmaceutical ink, polysorbate 80, povidone, purified water, sorbitol sorbitan solution

Questions or comments?

call 1-877-290-4008